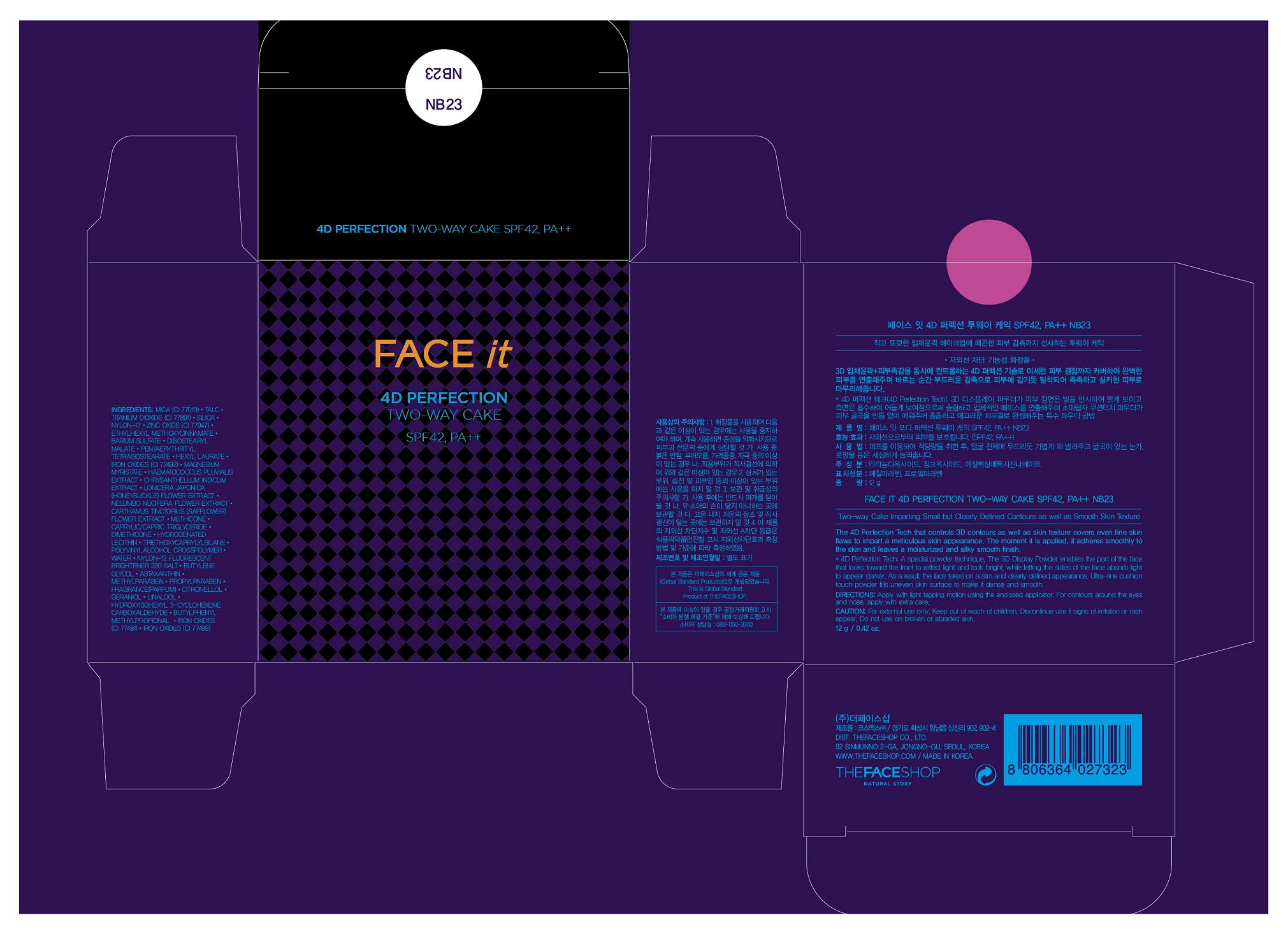 DRUG LABEL: FACE IT 4D PERPECT TWO-WAY CAKE NB23
NDC: 51523-116 | Form: POWDER
Manufacturer: THEFACESHOP CO., LTD
Category: otc | Type: HUMAN OTC DRUG LABEL
Date: 20110909

ACTIVE INGREDIENTS: TITANIUM DIOXIDE 13.96843 g/100 g; OCTINOXATE 3.5 g/100 g; ZINC OXIDE 4.41 g/100 g
INACTIVE INGREDIENTS: MICA; DIMETHICONE; TRIETHOXYCAPRYLYLSILANE; TALC; SILICON DIOXIDE; BARIUM SULFATE; HEXYL LAURATE; FERRIC OXIDE YELLOW; MEDIUM-CHAIN TRIGLYCERIDES; HYDROGENATED SOYBEAN LECITHIN; FERRIC OXIDE RED; METHYLPARABEN; MAGNESIUM MYRISTATE; FERROSOFERRIC OXIDE; PROPYLPARABEN; HAEMATOCOCCUS PLUVIALIS; WATER; BUTYLENE GLYCOL; ASTAXANTHIN; CHRYSANTHELLUM INDICUM TOP; LONICERA JAPONICA FLOWER; NELUMBO NUCIFERA FLOWER; SAFFLOWER

FACE IT 4D PERPECT TWO-WAY CAKE NB23

ACTIVE INGREDIENT

TITANIUM DIOXIDE (13.96843%)
OCTINOXATE (3.5%)
ZINC OXIDE (4.41%)

WARNINGS AND PRECAUTIONS

For external use only

Keep out of reach of children. Is swallowed, get medical help or contact a Poison Control Center right away.

WHEN USING

Keep out of eyes. Rinse with water to remove.

Stop use if a rash or irritation develops and lasts.

PACKAGE LABEL

FACE IT 4D PERPECT TWO-WAY CAKE NB23